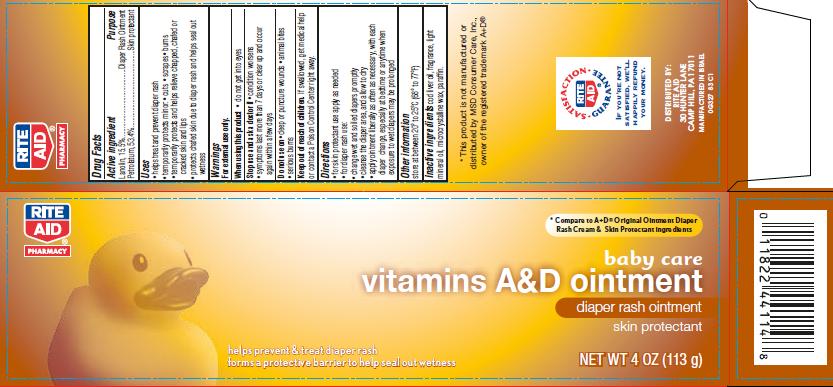 DRUG LABEL: Baby Care Vitamins A and D
NDC: 11822-3271 | Form: OINTMENT
Manufacturer: Rite Aid Corporation
Category: otc | Type: HUMAN OTC DRUG LABEL
Date: 20140307

ACTIVE INGREDIENTS: LANOLIN 15.5 g/100 g; PETROLATUM 53.4 g/100 g
INACTIVE INGREDIENTS: COD LIVER OIL; LIGHT MINERAL OIL; MICROCRYSTALLINE WAX; PARAFFIN

vitamins A&D ointment

Active ingredient

Lanolin, 15.5%
Petrolatum, 53.4%

Purpose

Diaper Rash Ointment
Skin protectant

Uses

- helps treat and prevent diaper rash
- temporarily protects minor:
  ● cuts
  ● scrapes
  ● burns
- temporarily protects and helps relieve chapped, chafed or cracked skin and lips
- protects chafed skin due to diaper rash and helps seal out wetness

Warnings

For external use only.

When using this product

- do not get into eyes

Stop use and ask a doctor if

- condition worsens
- symptoms last more than 7 days or clear up and occur again within a few days

Do Not Use

- deep or puncture wounds
- animal bites
- serious burns

Keep Out of Reach of Children.

If swallowed, get medical help or contact a Poison Control Center right away.

Directions

- for skin protectant use apply as needed
- for diaper rash use:
- change wet and soiled diapers promptly
- cleanse the diaper area, and allow to dry
- apply ointment liberally as often as necessary, with each diaper change, especially at bedtime or any time when exposure to wet diapers may be prolonged

Other Information

store at 20° to 25°C (68° to 77°F)

Inactive ingredients

cod liver oil, fragrance, light mineral oil, microcrystalline wax, paraffin.

Package/Label Principal Display Panel

baby care
vitamins
A&D ointment
diaper rash ointment

skin protectant

NET WT 4 OZ. (113 g)

SATISFACTION GUARANTEE
IF YOU’RE NOT SATISFIED, WE’LL HAPPILY REFUND YOUR MONEY.

DISTRIBUTED BY:
RITE AID,
30 HUNTER LANE
CAMP HILL, PA 17011

MANUFACTURED IN ISRAEL
0G327 83 T1

Carton Label